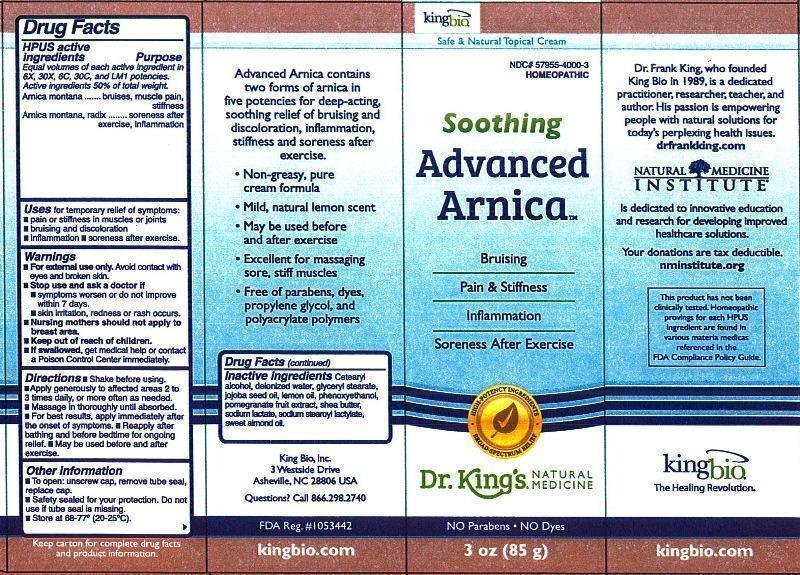 DRUG LABEL: Soothing Advanced Arnica
NDC: 57955-4000 | Form: CREAM
Manufacturer: King Bio Inc.
Category: homeopathic | Type: HUMAN OTC DRUG LABEL
Date: 20140929

ACTIVE INGREDIENTS: ARNICA MONTANA 6 [hp_X]/85 g; ARNICA MONTANA ROOT 6 [hp_X]/85 g
INACTIVE INGREDIENTS: ARNICA CHAMISSONIS FLOWER; CETOSTEARYL ALCOHOL; WATER; GLYCERYL MONOSTEARATE; JOJOBA OIL; LEMON OIL; PHENOXYETHANOL; POMEGRANATE; SHEA BUTTER; SODIUM LACTATE; SODIUM STEAROYL LACTYLATE; ALMOND OIL

Soothing Advanced Arnica™

ACTIVE INGREDIENT

Drug Facts__________________________________________________________________________________________________________

HPUS active ingredients: Arnica montana, Arnica montana, radix. Equal volumes of each active ingredient in 6X, 30X, 6C, 30C, and LM1 potencies. Active ingredients 50% of total weight.

INDICATIONS AND USAGE

Uses for temporary relief of symptoms:

- pain or stiffness in muscles or joints
- bruising and discoloration
- inflammation
- soreness after exercise

Warnings

- For external use only. Avoid contact with eyes and broken skin.
- Stop use and ask a doctor if •symptoms worsen or do not improve within 7 days. •skin irritation, redness or rash occurs.
- Nursing mothers should not apply to breast area.
- Keep out of reach of children.
- If swallowed, get medical help or contact a Poison Control Center immediately.

- Keep out of reach of children.

Directions

•Shake before using. •Apply generously to affected areas 2 to 3 times daily, or more often as needed. •Massage in thoroughly until absorbed. •For best results, apply immediately after the onset of symptoms. •Reapply after bathing and before bedtime for ongoing relief. •May be used before and after exercise.

Other information:

- To open: unscrew cap, remove tube seal, replace cap.
- Safety sealed for your protection.
- Do not use if tube seal is missing.
- Store at 68-77° (20-25°C).

INACTIVE INGREDIENT

Inactive ingredients: Cetearyl alcohol, deionized water, glyceryl stearate, jojoba seed oil, lemon oil, phenoxyethanol, pomegranate fruit extract, shea butter, sodium lactate, sodium stearoyl lactylate, sweet almond oil.

Drug Facts

____________________________________________________________________________________________________________________

HPUS active ingredients Purpose

Equal volumes of each active ingredient in 6X, 30X, 6C, and LM1 potencies.

Active ingredients 50% of total weight.

Arnica montana................................................bruises, muscle pain, stiffness

Arnica montana, radix.......................................soreness after exercise, inflammation